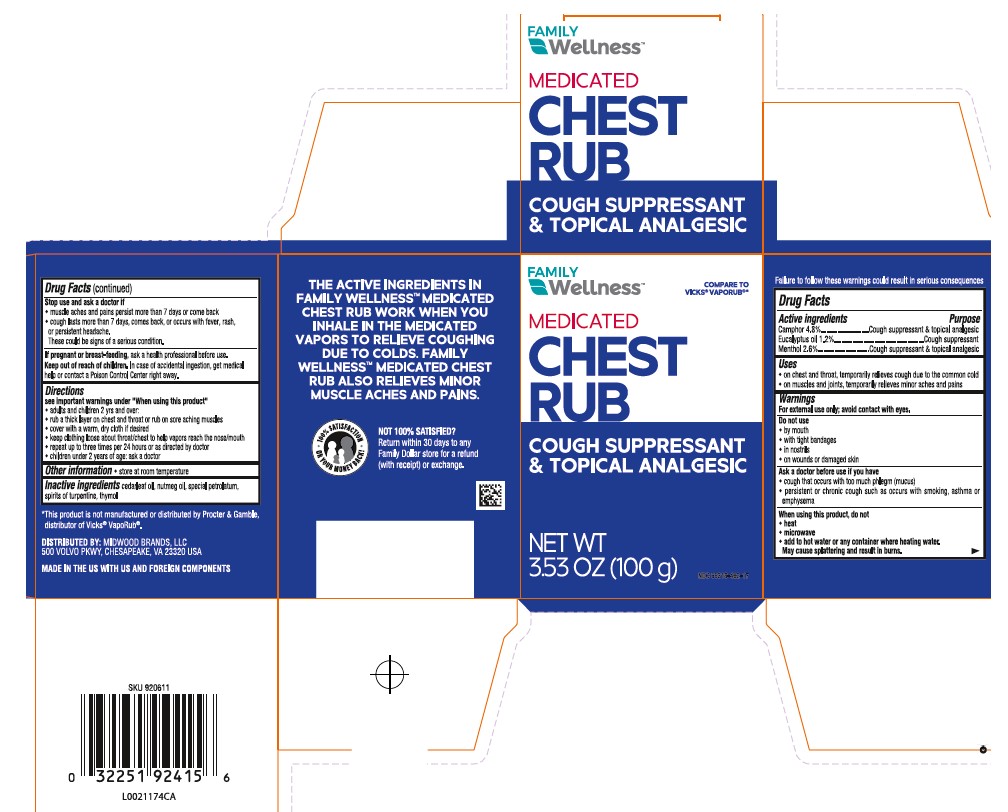 DRUG LABEL: Chest Rub
NDC: 55319-482 | Form: JELLY
Manufacturer: Family Dollar Stores, Inc
Category: otc | Type: HUMAN OTC DRUG LABEL
Date: 20260224

ACTIVE INGREDIENTS: CAMPHOR (NATURAL) 48 mg/1 g; EUCALYPTUS OIL 12 mg/1 g; MENTHOL 26 mg/1 g
INACTIVE INGREDIENTS: CEDAR LEAF OIL; NUTMEG OIL; PETROLATUM; TURPENTINE OIL; THYMOL

Family Wellness 248.001/248AI
Medicated Chest Rub

Warning

Failure to follow these warnings could result in serious consequences

Active ingredients

Camphor 4.8%

Eucalyptus oil 1.2%

Menthol 2.6%

Purpose

Cough suppressant & topical analgesic

Uses

- on chest and throat, temporarily relieves cough due to common cold
- on muscles and jonts, temporarily relieves minor aches and pains

Warnings

For external use only; avoid contact with eyes

Do not use

- by mouth
- with tight bandages
- in nostrils
- on wounds or damaged skin

Ask a doctor before use if you have

- cough that occurs with too much phlegm (mucus)
- persistent or chronic cough such as occurs with smoking, asthma or emphysema

When using this product, do not

- heat
- microwave
- add to hot water or any container where heating water.

May cause splattering and result in burns

Stop use and ask a doctor if

- muscle aches and pains persist more than 7 days or come back
- cough lasts more than 7 days, comes back, or occurs with fever, rash or persistent headache.

These could be signs of a serious condition.

If pregnant or breast-feeding,

ask a health professional before use.

Keep out of reach of children.

In case of accidental ingestion, get medical help or contact a Poison Control Center right away.

Directions

See important warning under "When using this product"

- adults & children 2 yrs & over:
- rub a thick layer on chest & throat or rub on sore aching muscles
- cover with warm, dry cloth if desired
- keep clothing loose about throat/chest to help vapors reach the nose/mouth
- repeat up to three times per 24 hours or as directed by doctor
- children under 2 years of age: ask a doctor

Other information

- store at room temperature

Inactive ingredients

cedarleaf oil, nutmeg oil, special petrolatum, spirits of turpentine, thymol

Disclaimer

*This product is not manufactured or distributed by Procter & Gamble, distributor of Vicks® VapoRub®.

Adverse Reactions

DISTRIBUTED BY: MIDWOOD BRANDS, LLC

500 VOLVO PKWY, CHESAPEAKE, VA 23320 USA

100% SATISFACTION OR YOUR MONEY BACK!

NOT 100% SATISFIED?

Return within 30 days to any Family Dollar store for a refund (with receipt) or exchange.

Claims

MADE IN THE US WITH US AND FOREIGN COMPONENTS

THE ACTIVE INGREDIENTS IN FAMILY WELLNESS™ MEDICATED CHEST RUB WORK WHEN YOU INHALE THE MEDICATED VAPORS TO RELIEVE COUGHING DUE TO COLDS. FAMILY WELLNESS™ MEDICATED CHEST RUB ALSO RELIEVES MINOR MUSCLE ACHES AND PAINS.

Principal Panel Display

FAMILY Wellness™

COMPARE TO VICKS®VAPORUB®*

MEDICATED CHEST RUB

COUGH SUPPRESSANT & TOPICAL ANALGESIC

NET WT 3.53 OZ (100 g)

NDC 55319-482-17